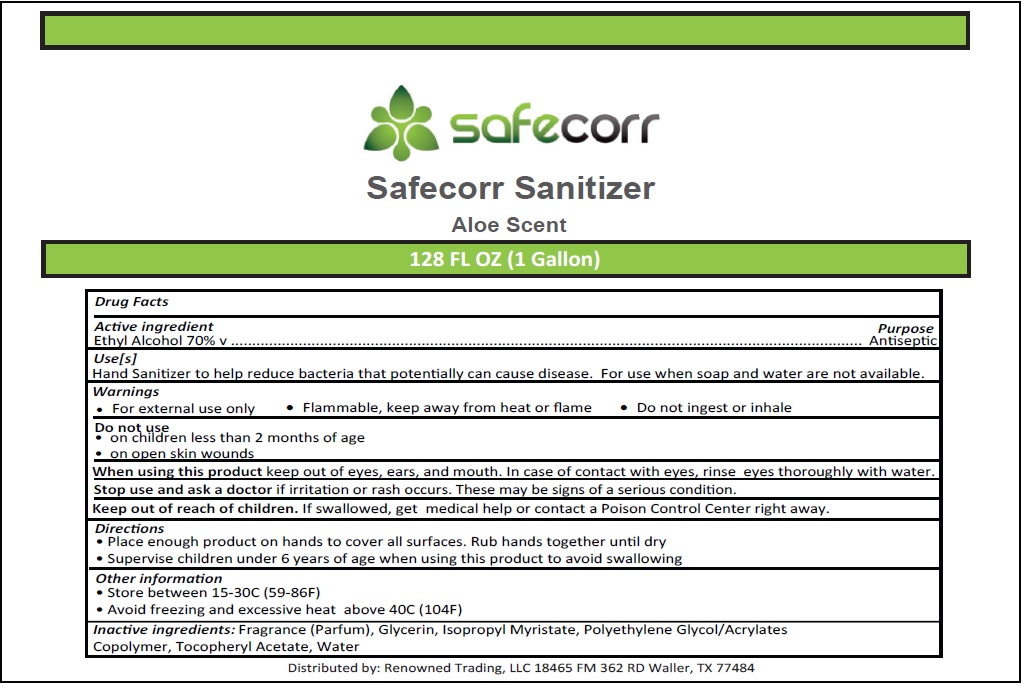 DRUG LABEL: Safecorr Sanitizer
NDC: 74837-003 | Form: GEL
Manufacturer: Renowned Chemical Solutions LLC
Category: otc | Type: HUMAN OTC DRUG LABEL
Date: 20200715

ACTIVE INGREDIENTS: ALCOHOL 70 mL/100 mL
INACTIVE INGREDIENTS: GLYCERIN; ISOPROPYL MYRISTATE; POLYETHYLENE GLYCOL, UNSPECIFIED; BUTYL ACRYLATE/METHYL METHACRYLATE/METHACRYLIC ACID COPOLYMER (18000 MW); .ALPHA.-TOCOPHEROL ACETATE; WATER

Safecorr Sanitizer

Active ingredient

Ethyl Alcohol 70% v/v

Purpose

Antiseptic

Use[s]

Hand Sanitizer to help reduce bacteria that potentially can cause disease. For use when soap and water are not available.

Warnings

• For external use only • Flammable, keep away from heat or flame • Do not use ingest or inhale

Do not use

• on children less than 2 months of age
• on open skin wounds

When using this product keep out of eyes, ears, and mouth. In case of contact with eyes, rinse eyes thoroughly with water.

Stop use and ask a doctor if irritation or rash occurs. These may be signs of a serious condition.

Keep out of reach of children. If swallowed, get medical help or contact a Poison Control Center right away.

Directions

• Place enough product on hands to cover all surfaces. Rub hands together until dry

• Supervise children under 6 years of age when using this product to avoid swallowing

Other information

• Store between 15-30C (59-86F)

• Avoid freezing and excessive heat above 40C (104F)

INACTIVE INGREDIENT

Inactive ingredients: Fragrance (Parfum), Glycerin, Isopropyl Myristate, Polyethylene Glycol/Acrylates Copolymer, Tocopheryl Acetate, Water

Aloe Scent

Distributed by: Renowned Trading, LLC 18465 FM 362 RD Waller, TX 77484